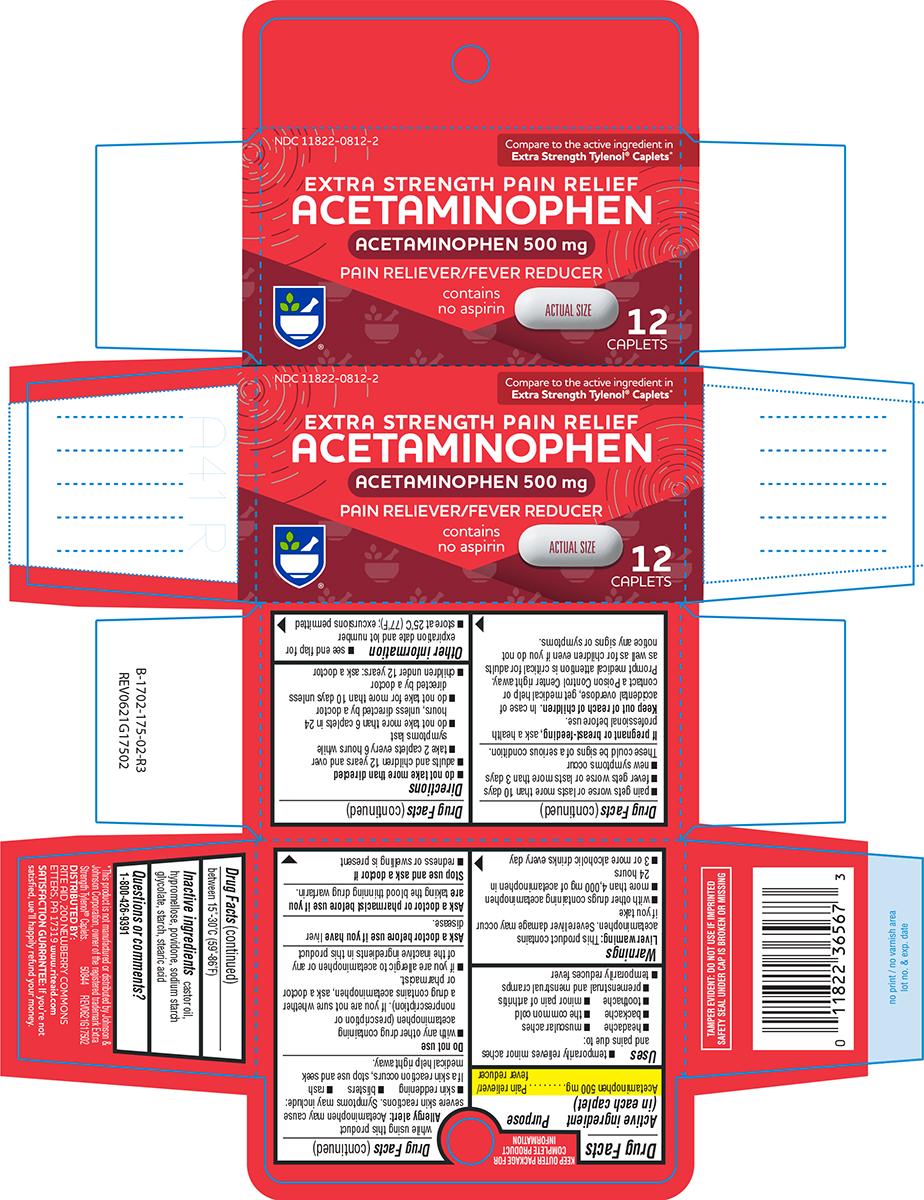 DRUG LABEL: Pain Relief
NDC: 11822-0812 | Form: TABLET, FILM COATED
Manufacturer: Rite Aid Corporation
Category: otc | Type: HUMAN OTC DRUG LABEL
Date: 20250916

ACTIVE INGREDIENTS: ACETAMINOPHEN 500 mg/1 1
INACTIVE INGREDIENTS: CASTOR OIL; HYPROMELLOSE, UNSPECIFIED; POVIDONE, UNSPECIFIED; SODIUM STARCH GLYCOLATE TYPE A POTATO; STARCH, CORN; STEARIC ACID

Pain Reliever

Active ingredient (in each caplet)

Acetaminophen 500 mg

Purpose

Pain reliever/fever reducer

Uses

- temporarily relieves minor aches and pains due to:
  - headache
  - muscular aches
  - backache
  - the common cold
  - toothache
  - minor pain of arthritis
  - premenstrual and menstrual cramps
- temporarily reduces fever

Warnings

Liver warning: This product contains acetaminophen. Severe liver damage may occur if you take

- with other drugs containing acetaminophen
- more than 4,000 mg of acetaminophen in 24 hours
- 3 or more alcoholic drinks every day while using this product

Allergy alert: Acetaminophen may cause severe skin reactions. Symptoms may include:

- skin reddening
- blisters
- rash

If a skin reaction occurs, stop use and seek medical help right away.

Do not use

- with any other drug containing acetaminophen (prescription or nonprescription). If you are not sure whether a drug contains acetaminophen, ask a doctor or pharmacist.
- if you are allergic to acetaminophen or any of the inactive ingredients in this product

Ask a doctor before use if you have

liver disease.

Ask a doctor or pharmacist before use if you are

taking the blood thinning drug warfarin.

Stop use and ask a doctor if

- redness or swelling is present
- pain gets worse or lasts more than 10 days
- fever gets worse or lasts more than 3 days
- new symptoms occur

These could be signs of a serious condition.

If pregnant or breast-feeding,

ask a health professional before use.

Keep out of reach of children.

In case of accidental overdose, get medical help or contact a Poison Control Center right away. Prompt medical attention is critical for adults as well as for children even if you do not notice any signs or symptoms.

Directions

- do not take more than directed
- adults and children 12 years and over
  - take 2 caplets every 6 hours while symptoms last
  - do not take more than 6 caplets in 24 hours, unless directed by a doctor
  - do not take for more than 10 days unless directed by a doctor
- children under 12 years: ask a doctor

Other information

- see end flap for expiration date and lot number
- store at 25°C (77°F); excursions permitted between 15°-30°C (59°-86°F)

Inactive ingredients

castor oil, hypromellose, povidone, sodium starch glycolate, starch, stearic acid

Questions or comments?

1-800-426-9391

Principal Display Panel

NDC 11822-0812-2

Compare to the active ingredient in
Extra Strength Tylenol® Caplets*

EXTRA STRENGTH PAIN RELIEF
ACETAMINOPHEN

ACETAMINOPHEN 500 mg
PAIN RELIEVER/FEVER REDUCER

contains no aspirin

ACTUAL SIZE

12
CAPLETS

TAMPER EVIDENT: DO NOT USE IF IMPRINTED
SAFETY SEAL UNDER CAP IS BROKEN OR MISSING

*This product is not manufactured or distributed by
Johnson & Johnson Corporation, owner of the
registered trademark Extra Strength Tylenol® Caplets.
50844 REV0621G17502

DISTRIBUTED BY:
RITE AID, 200 NEWBERRY COMMONS
ETTERS, PA 17319 www.riteaid.com

SATISFACTION
GUARANTEE
If you're not satisfied, we'll
happily refund your money

Rite Aid 44-175
.